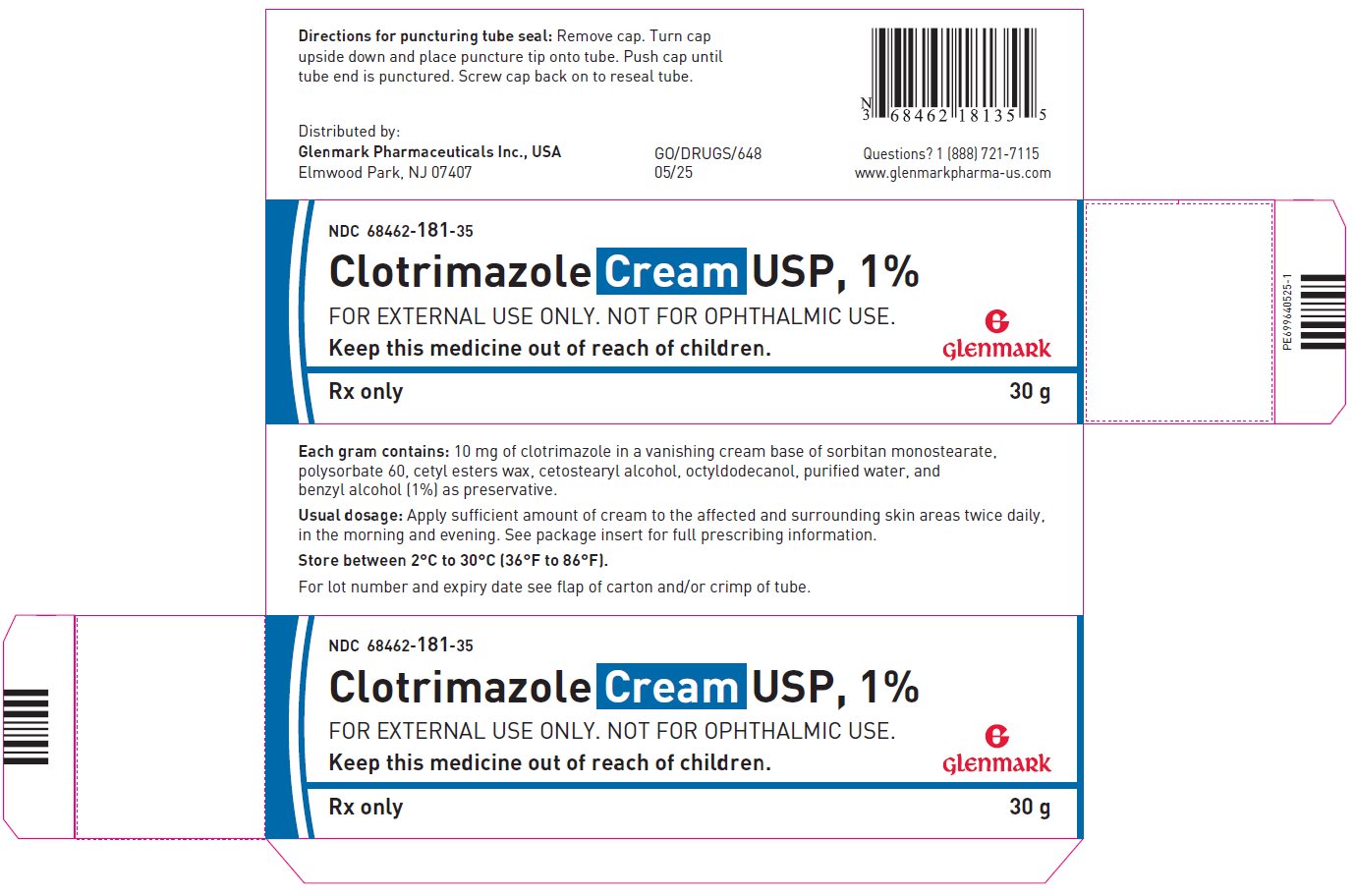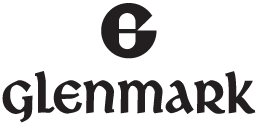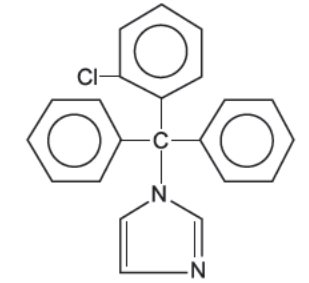 DRUG LABEL: Clotrimazole
NDC: 68462-181 | Form: CREAM
Manufacturer: Glenmark Pharmaceuticals Inc., USA
Category: prescription | Type: HUMAN PRESCRIPTION DRUG LABEL
Date: 20260130

ACTIVE INGREDIENTS: CLOTRIMAZOLE 10 mg/1 g
INACTIVE INGREDIENTS: BENZYL ALCOHOL; WATER; CETOSTEARYL ALCOHOL; OCTYLDODECANOL; POLYSORBATE 60; SORBITAN

Clotrimazole Cream USP, 1%

For external use only
Not for Ophthalmic Use

Rx only

DESCRIPTION

Clotrimazole cream USP, 1% contains clotrimazole USP, a synthetic antifungal agent having the chemical name {1-(o-Chloro-α, α-diphenylbenzyl)imidazole}; the molecular formula C22H17ClN2; a molecular weight of 344.84; and the structural formula:

Clotrimazole USP is an odorless, white crystalline substance. It is practically insoluble in water, sparingly soluble in ether and very soluble in polyethylene glycol 400, ethanol and chloroform.

Each gram of clotrimazole cream USP contains 10 mg clotrimazole USP, dispersed in a vanishing cream base of sorbitan monostearate, polysorbate 60, cetyl esters wax, cetostearyl alcohol, octyldodecanol, purified water, and benzyl alcohol (1%) as preservative.

CLINICAL PHARMACOLOGY

Clotrimazole is a broad-spectrum antifungal agent that is used for the treatment of dermal infections caused by various species of pathogenic dermatophytes, yeasts, and Malassezia furfur. The primary action of clotrimazole is against dividing and growing organisms.

In vitro, clotrimazole exhibits fungistatic and fungicidal activity against isolates of Trichophyton rubrum, Trichophyton mentagrophytes, Epidermophyton floccosum, Microsporum canis and Candida species including Candida albicans. In general, the in vitro activity of clotrimazole corresponds to that of tolnaftate and griseofulvin against the mycelia of dermatophytes (Trichophyton, Microsporum, and Epidermophyton), and to that of the polyenes (amphotericin B and nystatin) against budding fungi (Candida). Using an in vivo (mouse) and an in vitro (mouse kidney homogenate) testing system, clotrimazole and micronazole were equally effective in preventing the growth of the pseudomycelia and mycelia of Candida albicans.

Strains of fungi having a natural resistance to clotrimazole are rare. Only a single isolate of Candida guilliermondi has been reported to have primary resistance to clotrimazole.

No single-step or multiple-step resistance to clotrimazole has developed during successive passages of Candida albicans and Trichophyton mentagrophytes. No appreciable change in sensitivity was detected after successive passage of isolates of C. albicans, C. krusei, or C. pseudotropicalis in liquid or solid media containing clotrimazole. Also, resistance could not be developed in chemically induced mutant strains of polyene-resistant isolates of C. albicans. Slight, reversible resistance was noted in three isolates of C. albicans tested by one investigator. There is a single report that records the clinical emergence of C. albicans strain with considerable resistance to flucytosine and micronazole, and with cross-resistance to clotrimazole, the strain remained sensitive to nystatin and amphotericin B.

In studies of the mechanism of action, the minimum fungicide concentration of clotrimazole caused leakage of intracellular phosphorus compounds into the ambient medium with concomitant breakdown of cellular nucleic acids and accelerated potassium efflux. Both these events began rapidly and extensively after addition of the drug.

Clotrimazole appears to be well absorbed in humans following oral administration and is eliminated mainly as inactive metabolites. Following topical and vaginal administration, however, clotrimazole appears to be minimally absorbed.

Six hours after the application of radioactive clotrimazole 1% cream and 1% solution onto intact and acutely inflamed skin, the concentration of clotrimazole varied from 100 mcg/cm^3 in the stratum corneum to 0.5 to 1 mcg/cm^3 in the stratum reticulare, and 0.1 mcg/cm^3 in the subcutis. No measurable amount of radioactivity (≤0.001 mcg/mL) was found in the serum within 48 hours after application under occlusive dressing of 0.5 mL of the solution or 0.8 g of the cream. Only 0.5% or less of the applied radioactivity was excreted in the urine.

Following intravaginal administration of 100 mg ^14C-clotrimazole vaginal tablets to nine adult females, an average peak serum level, corresponding to only 0.03 μg equivalent/mL of clotrimazole, was reached one to two days after application. After intravaginal administration of 5 g of 1% ^14C-clotrimazole vaginal cream containing 50 mg active drug, to five subjects (one with candidal colpitis), serum levels corresponding to approximately 0.01 μg equivalents/mL were reached between 8 and 24 hours after application.

INDICATIONS AND USAGE

Clotrimazole cream USP is indicated for the topical treatment of candidiasis due to Candida albicans and tinea versicolor due to Malassezia furfur.

Clotrimazole is also available as a nonprescription item which is indicated for the topical treatment of the following dermal infections: tinea pedis, tinea cruris, and tinea corporis due to Trichophyton rubrum, Trichophyton mentagrophytes, Epidermophyton floccosum, and Microsporum canis.

CONTRAINDICATIONS

Clotrimazole cream is contraindicated in individuals sensitive to its components.

WARNINGS

Clotrimazole cream is not for ophthalmic use.

PRECAUTIONS

General:

If irritation or sensitivity develops with the use of clotrimazole cream, treatment should be discontinued and appropriate therapy instituted.

Information for Patients:

The patient should be advised to:

1. Use the medication for the full treatment time even though the symptoms may have improved. Notify the physician if there is no improvement after four weeks of treatment.
2. Inform the physician if the area of application shows signs of increased irritation (redness, itching, burning, blistering, swelling, oozing) indicative of possible sensitization.
3. Avoid the use of occlusive wrappings or dressings.
4. Avoid sources of infection or reinfection.

Laboratory Tests

If there is lack of response to clotrimazole cream, appropriate microbiological studies should be repeated to confirm the diagnosis and rule out other pathogens before instituting another course of antimycotic therapy.

Drug Interactions

Synergism or antagonism between clotrimazole and nystatin, or amphotericin B, or flucytosine against strains of C. albicans has not been reported.

Carcinogenesis, Mutagenesis, Impairment of Fertility

An 18-month oral dosing study with clotrimazole in rats has not revealed any carcinogenic effect.

In tests for mutagenesis, chromosomes of the spermatophores of Chinese hamsters which had been exposed to clotrimazole were examined for structural changes during the metaphase. Prior to testing, the hamsters had received five oral clotrimazole doses of 100 mg/kg body weight. The results of this study showed that clotrimazole had no mutagenic effect.

Usage in Pregnancy: Pregnancy Category B

The disposition of ^14C-clotrimazole has been studied in humans and animals. Clotrimazole is very poorly absorbed following dermal application or intravaginal administration to humans. (See CLINICAL PHARMACOLOGY)

In clinical trials, use of vaginally applied clotrimazole in pregnant women in their second and third trimesters has not been associated with ill effects. There are, however, no adequate and well-controlled studies in pregnant women during the first trimester of pregnancy.

Studies in pregnant rats with intravaginal doses up to 100 mg/kg have revealed no evidence of harm to the fetus due to clotrimazole.

High oral doses of clotrimazole in rats and mice ranging from 50 to 120 mg/kg resulted in embroyotoxicity (possible secondary to maternal toxicity), impairment of mating, decreased litter size and number of viable young and decreased pup survival to weaning. However, clotrimazole was not teratogenic in mice, rabbits and rats at oral doses up to 200, 180 and 100 mg/kg, respectively. Oral absorption in the rat amounts to approximately 90% of the administered dose.

Because animal reproduction studies are not always predictive of human response, this drug should be used only if clearly indicated during the first trimester of pregnancy.

Nursing Mothers

It is not known whether this drug is excreted in human milk, caution should be exercised when clotrimazole is used by a nursing woman.

Pediatric Use

Safety and effectiveness in children have been established for clotrimazole when used as indicated and in the recommended dosage.

ADVERSE REACTIONS

The following adverse reactions have been reported in connection with the use of this product: erythema, stinging, blistering, peeling, edema, pruritis, urticaria, burning, and general irritation of the skin.

OVERDOSAGE

Acute overdosage with topical application of clotrimazole is unlikely and would not be expected to lead to a life-threatening situation.

DOSAGE AND ADMINISTRATION

Gently massage sufficient clotrimazole cream into the affected and surrounding skin areas twice a day, in the morning and evening.

Clinical improvement, with relief of pruritis, usually occurs within the first week of treatment with clotrimazole cream. If the patient shows no clinical improvement after four weeks of treatment with clotrimazole cream, the diagnosis should be reviewed.

HOW SUPPLIED

Clotrimazole cream USP, 1% is supplied in 15, 30, 45 and (2 x 45) gram tubes.

NDC 68462-181-17 (15 g)
NDC 68462-181-35 (30 g)
NDC 68462-181-47 (45 g)
NDC 68462-181-48 (2 x 45 g)

STORAGE AND HANDLING

Store between 2°C- 30°C(36°F -86°F).

Distributed by:

Glenmark Pharmaceuticals Inc., USA
Elmwood Park, NJ 07407

Questions? 1 (888)721-7115
www.glenmarkpharma-us.com

May 2025

Principal Display Panel

NDC 68462-181-35
Clotrimazole Cream USP, 1%
For external use only. Not for ophthalmic use.